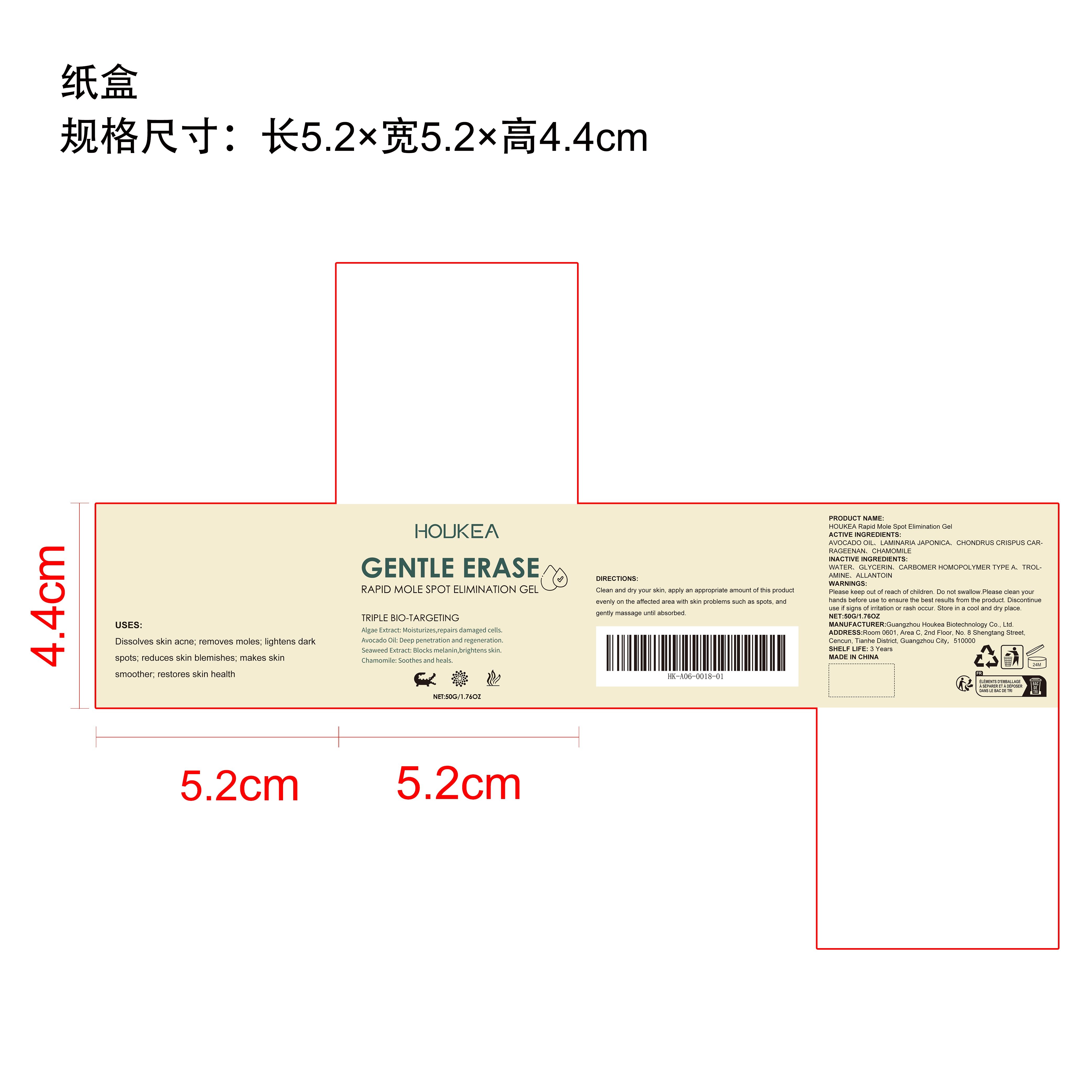 DRUG LABEL: HOUKEA Rapid Mole Spot Elimination Gel
NDC: 84984-006 | Form: GEL
Manufacturer: Guangzhou Houkea Biotechnology Co., Ltd.
Category: otc | Type: HUMAN OTC DRUG LABEL
Date: 20251127

ACTIVE INGREDIENTS: LAMINARIA JAPONICA 0.01 mg/50 mg; CHAMOMILE 0.01 mg/50 mg; AVOCADO OIL 0.01 mg/50 mg; CHONDRUS CRISPUS CARRAGEENAN 0.01 mg/50 mg
INACTIVE INGREDIENTS: ALLANTOIN 0.01 mg/50 mg; GLYCERIN 4 mg/50 mg; WATER 45.75 mg/50 mg; CARBOMER HOMOPOLYMER TYPE A 0.1 mg/50 mg; TROLAMINE 0.1 mg/50 mg

ACTIVE INGREDIENT

AVOCADO OIL、LAMINARIA JAPONICA、CHONDRUS CRISPUS CARRAGEENAN、CHAMOMILE

WHEN USING

Clean and dry your skin, apply an appropriate amount of this product evenly on the affected area with skin problems such as spots, and gently massage until absorbed.

PURPOSE

Dissolves skin acne; removes moles; lightens dark spots; reduces skin blemishes; makes skin smoother; restores skin health

WARNINGS

Please keep out of reach of children. Do not swallow.Please clean your hands before use to ensure the best results from the product. Discontinue use if signs of irritation or rash occur. Store in a cool and dry place.

DO NOT USE

Discontinue use if signs of irritation or rash occur.

STOP USE

Discontinue use if signs of irritation or rash occur.

KEEP OUT OF REACH OF CHILDREN

Please keep out of reach of children. Do not swallow.

STORAGE AND HANDLING

Store in a cool and dry place.

INACTIVE INGREDIENT

WATER、GLYCERIN、CARBOMER HOMOPOLYMER TYPE A、TROLAMINE、ALLANTOIN

DOSAGE AND ADMINISTRATION

Clean and dry your skin, apply an appropriate amount of this product evenly on the affected area with skin problems such as spots, and gently massage until absorbed.

INDICATIONS AND USAGE

Rapid Mole Spot Elimination Gel；Mole Remover Gel；Spot Gel